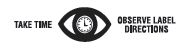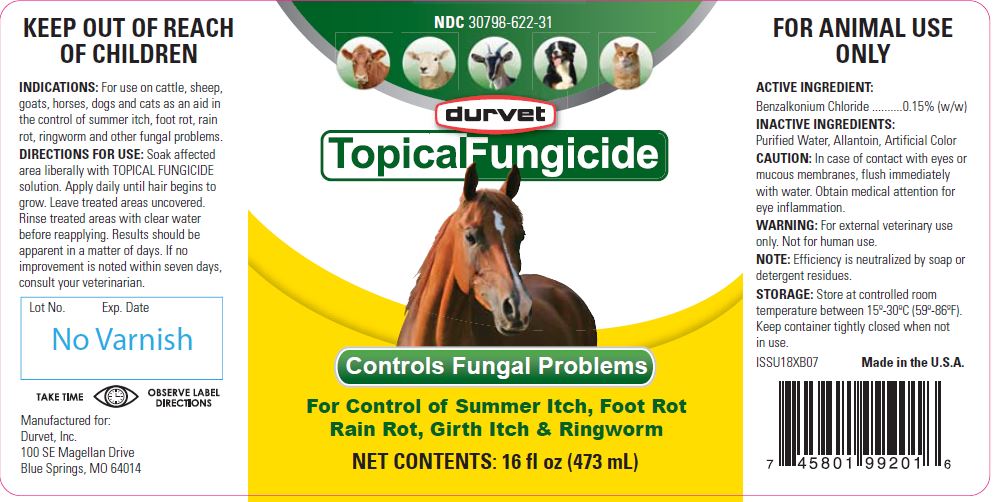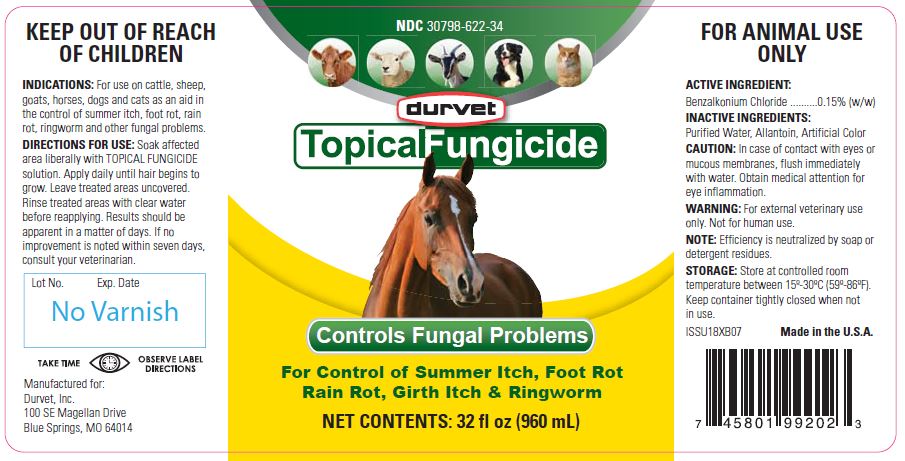 DRUG LABEL: Topical Fungicide
NDC: 30798-622 | Form: SOLUTION
Manufacturer: Durvet, Inc.
Category: animal | Type: OTC ANIMAL DRUG LABEL
Date: 20190221

ACTIVE INGREDIENTS: BENZALKONIUM CHLORIDE 3.09 mg/1 mL

Topical Fungicide

PURPOSE

Controls Fungal Problems

For Control of Summer Itch, Foot Rot
Rain Rot, Girth Itch & Ringworm

KEEP OUT OF REACH OF CHILDREN

INDICATIONS:

For use on cattle, sheep, goats, horses, dogs and cats as an aid in the control of summer itch, foot rot, rain rot, ringworm and other fungal problems.

DIRECTIONS FOR USE:

Soak affected area liberally with TOPICAL FUNGICIDE solution. Apply daily until hair begins to grow. Leave treated areas uncovered.
Rinse treated areas with clear water before reapplying. Results should be apparent in a matter of days. If no improvement is noted within seven days, consult your veterinarian.

PRECAUTIONS

FOR ANIMAL USE ONLY

ACTIVE INGREDIENT:

Benzalkonium Chloride ..........0.15% (w/w)

INACTIVE INGREDIENTS:

Purified Water, Allantoin, Artificial Color

CAUTION:

In case of contact with eyes or mucous membranes, flush immediately with water. Obtain medical attention for eye inflammation.

WARNING:

For external veterinary use only. Not for human use.

NOTE:

Efficiency is neutralized by soap or detergent residues.

STORAGE:

Store at controlled room temperature between 15°-30°C (59°-86°F). Keep container tightly closed when not in use.

Net Contents:

16 fl oz (473 mL)

32 fl oz (960 mL)

INFORMATION FOR OWNERS/CAREGIVERS

Made in the U.S.A.

Manufactured for:
Durvet, Inc.
100 SE Magellan Drive
Blue Springs, MO 64014